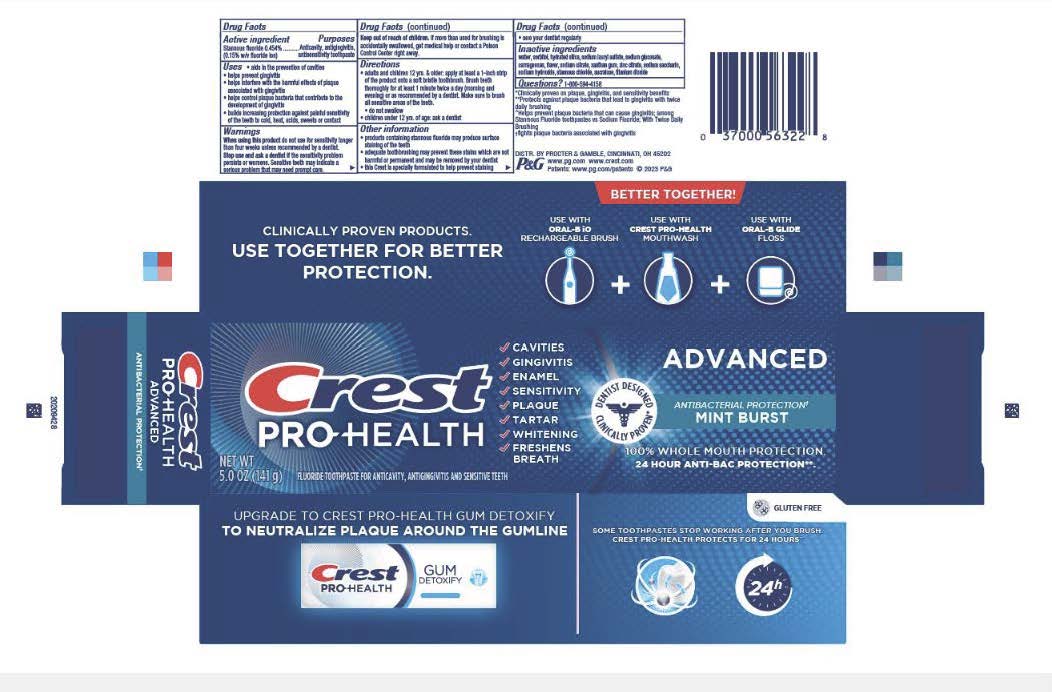 DRUG LABEL: Crest
NDC: 69423-857 | Form: PASTE, DENTIFRICE
Manufacturer: The Procter & Gamble Manufacturing Company
Category: otc | Type: HUMAN OTC DRUG LABEL
Date: 20260106

ACTIVE INGREDIENTS: STANNOUS FLUORIDE 1.4 mg/1 g
INACTIVE INGREDIENTS: SUCRALOSE; STANNOUS CHLORIDE; WATER; HYDRATED SILICA; CARRAGEENAN; SODIUM GLUCONATE; XANTHAN GUM; ZINC CITRATE; SODIUM LAURYL SULFATE; SORBITOL; SODIUM HYDROXIDE; SACCHARIN SODIUM; TITANIUM DIOXIDE; SODIUM CITRATE

Crest Pro-Health Advanced Antibacterial Protection

Drug Facts

Active ingredient

Stannous fluoride 0.454%

(0.14% w/v fluoride ion)

Purposes

Anticavity, antigingivitis antisensitivity toothpaste

Uses

- aids in the prevention of cavities
- helps prevent gingivitis
- helps interfere with the harmful effects of plaque associated with gingivitis
- helps control plaque bacteria that contribute to the development of gingivitis
- builds increasing protection against painful sensitivity of the teeth to cold, heat, acids, sweets, or contact

WARNINGS

When using this product do not use for sensitivity longer than four weeks unless recommended by a dentist.

Stop use and ask a dentist if the sensitivity problem persists or worsens. Sensitive teeth may indicate a serious problem that may need prompt care.

Keep out of reach of children. If more than used for brushing is accidentally swallowed, get medical help or contact a Poison Control Center right away.

Directions

- adults and children 12 yrs. & older: apply at least a 1-inch strip of the product onto a soft bristle toothbrush. Brush teeth thoroughly for at least 1 minute twice a day (morning and evening) or as recommended by a dentist. Make sure to brush all sensitive areas of the teeth.
- do not swallow
- children under 12 yrs. of age: ask a dentist

Other information

- products containing stannous fluoride may produce surface staining of the teeth
- adequate toothbrushing may prevent these stains which are not harmful or permanent and may be removed by your dentist
- this Crest is specially formulated to help prevent staining
- see your dentist regularly

Inactive ingredients

water, sorbitol, hydrated silica, sodium lauryl sulfate, sodium gluconate, carrageenan, flavor, sodium citrate, xanthan gum, zinc citrate, sodium saccharin, sodium hydroxide, stannous chloride, sucralose, titanium dioxide

Questions?

1-800-594-4158

DISTR. BY PROCTER & GAMBLE,

CINCINNATI, OH 45202

Principal Display Panel - 141 g tube in carton

CREST

PRO-HEALTH

FLUORIDE TOOTHPASTE FOR

ANTICAVITY AND ANTIGINGIVITIS AND SENSITIVE TEETH

NET WT 5.0 OZ (141 g)

… CAVITIES
… GINGIVITIS
… ENAMEL
… SENSITIVITY
… PLAQUE
… TARTAR
… WHITENING
… FRESHENS
BREATH

DENTIST DESIGNED

CLINICALLY PROVEN

ADVANCED

ANTIBACTERIAL PROTECTION

MINT BURST

100% WHOLE MOUTH PROTECTION

24 HOUR ANTI-BAC PROTECTION